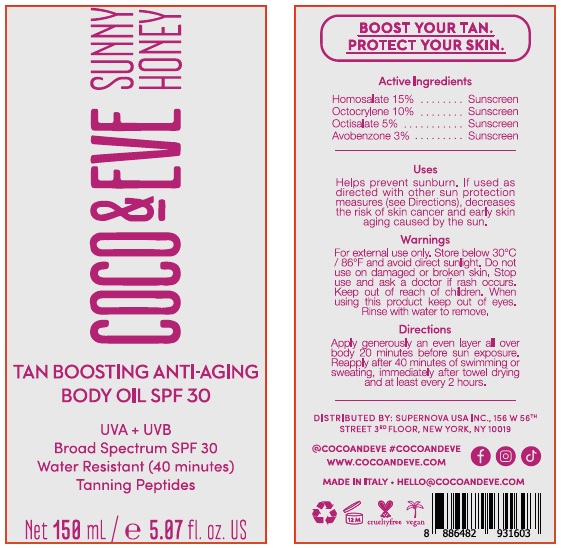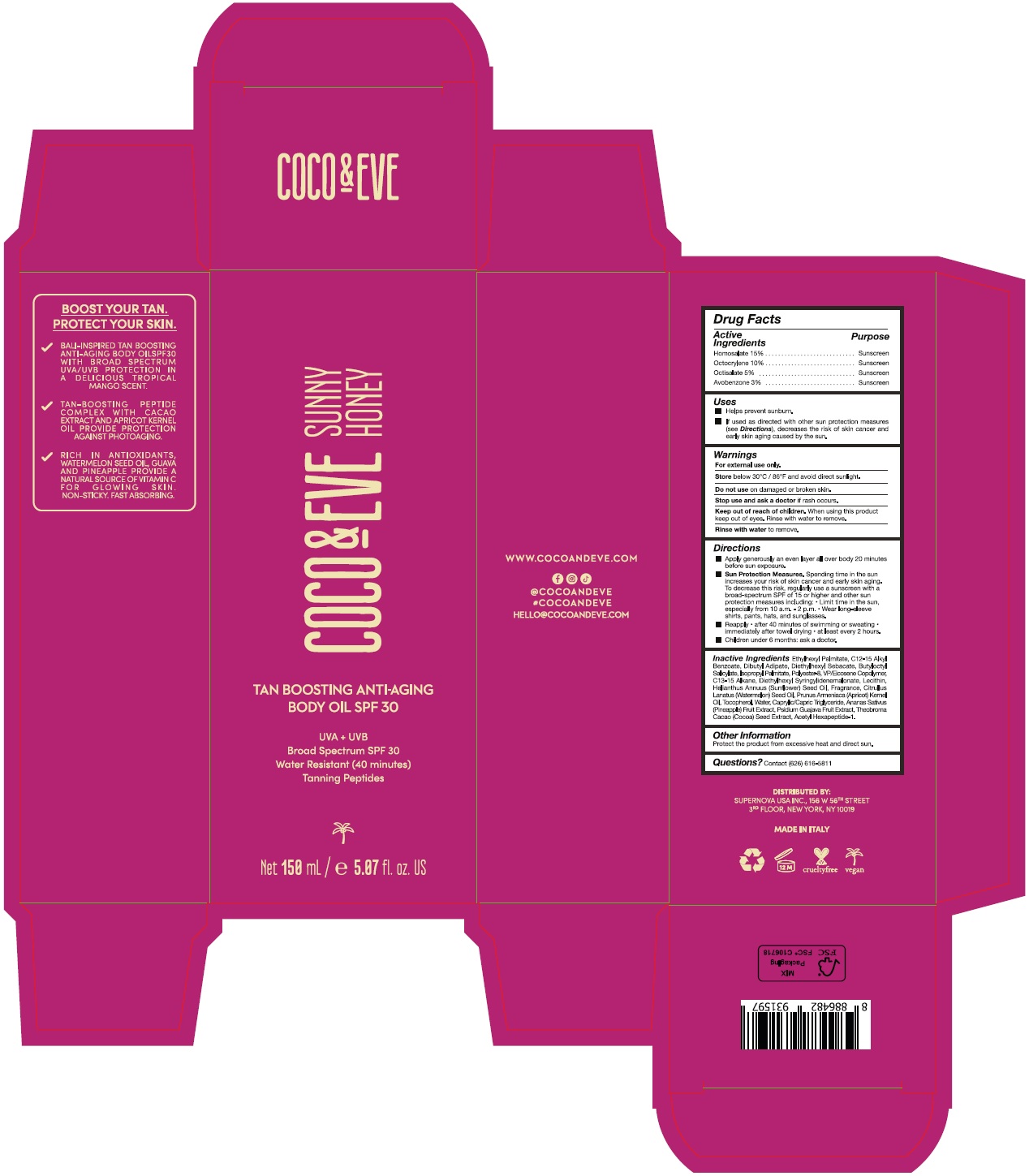 DRUG LABEL: coco and eve tan boosting anti-aging body oil spf 30
NDC: 82931-008 | Form: LOTION
Manufacturer: Supernova USA Inc.
Category: otc | Type: HUMAN OTC DRUG LABEL
Date: 20231116

ACTIVE INGREDIENTS: HOMOSALATE 15 g/100 mL; OCTOCRYLENE 10 g/100 mL; OCTISALATE 5 g/100 mL; AVOBENZONE 3 g/100 mL
INACTIVE INGREDIENTS: ETHYLHEXYL PALMITATE; ALKYL (C12-15) BENZOATE; DIBUTYL ADIPATE; DIETHYLHEXYL SEBACATE; BUTYLOCTYL SALICYLATE; ISOPROPYL PALMITATE; POLYESTER-8 (1400 MW, CYANODIPHENYLPROPENOYL CAPPED); VINYLPYRROLIDONE/EICOSENE COPOLYMER; C13-15 ALKANE; DIETHYLHEXYL SYRINGYLIDENEMALONATE; LECITHIN, SOYBEAN; SUNFLOWER OIL; ETHYL VANILLIN; VANILLIN; OCTAHYDROCOUMARIN; PIPERONAL; ETHYL MALTOL; SANDALORE; HEXYL SALICYLATE; 6,6-DIMETHOXY-2,5,5-TRIMETHYL-2-HEXENE; ETHYL LINALOOL; ISOCYCLEMONE E; BUTYLATED HYDROXYTOLUENE; .DELTA.-DAMASCONE; HEXAMETHYLINDANOPYRAN; .BETA.-DAMASCENONE; METHYL 2-NONYNOATE; WATERMELON SEED OIL; APRICOT KERNEL OIL; TOCOPHEROL; WATER; MEDIUM-CHAIN TRIGLYCERIDES; PINEAPPLE; GUAVA; COCOA; ACETYL HEXAPEPTIDE-1

COCO & EVE TAN BOOSTING ANTI-AGING BODY OIL SPF 30

Drug Facts

Active Ingredients
Homosalate 15%
Octocrylene 10%
Octisalate 5%
Avobenzone 3%

Purpose
Sunscreen

Uses

- Helps prevent sunburn.
- If used as directed with other sun protection measures (see Directions), decreases the risk of skin cancer and early skin aging caused by the sun.

Warnings

For external use only.

Store below 30°C / 86°F and avoid direct sunlight.

Do not use on damaged or broken skin.

Stop use and ask a doctor if rash occurs.

Keep out of reach of children. When using this product keep out of eyes. Rinse with water to remove.

Rinse with water to remove.

Directions

- Apply generously an even layer all over body 20 minutes before sun exposure.
- Sun Protection Measures. Spending time in the sun increases your risk of skin cancer and early skin aging. To decrease this risk, regularly use a sunscreen with a broad-spectrum SPF of 15 or higher and other sun protection measures including:
  - Limit time in the sun, especially from 10 a.m. - 2 p.m.
  - Wear long-sleeve shirts, pants, hats, and sunglasses.
- Reapply
  - after 40 minutes of swimming or sweating
  - immediately after towel drying
  - at least every 2 hours.
- Children under 6 months: ask a doctor.

INACTIVE INGREDIENT

Inactive Ingredients Ethylhexyl Palmitate, C12-15 Alkyl Benzoate, Dibutyl Adipate, Diethylhexyl Sebacate, Butyloctyl Salicylate, Isopropyl Palmitate, Polyester-8, VP/Eicosene Copolymer, C13-15 Alkane, Diethylhexyl Syringylidenemalonate, Lecithin, Helianthus Annuus (Sunflower) Seed Oil, Fragrance, Citrullus Lanatus (Watermelon) Seed Oil, Prunus Armeniaca (Apricot) Kernel Oil, Tocopherol, Water, Caprylic/Capric Triglyceride, Ananas Sativus (Pineapple) Fruit Extract, Psidium Guajava Fruit Extract, Theobroma Cacao (Cocoa) Seed Extract, Acetyl Hexapeptide-1.

Other Information

Protect the product from excessive heat and direct sun.

Questions? Contact (626) 616-5811

PRINCIPAL DISPLAY PANEL

COCO & EVE

SUNNY
HONEY

TAN BOOSTING ANTI-AGING

BODY OIL SPF 30

UVA + UVB

Broad Spectrum SPF 30

Water Resistant (40 minutes)

Tanning Peptides

Net 150 mL / e 5.07 fl. oz. US

COCO & EVE

SUNNY
HONEY

TAN BOOSTING ANTI-AGING

BODY OIL SPF 30

UVA + UVB

Broad Spectrum SPF 30

Water Resistant (40 minutes)

Tanning Peptides

Net 150 mL / e 5.07 fl. oz. US